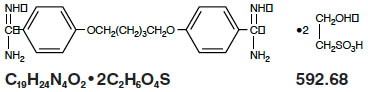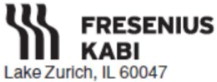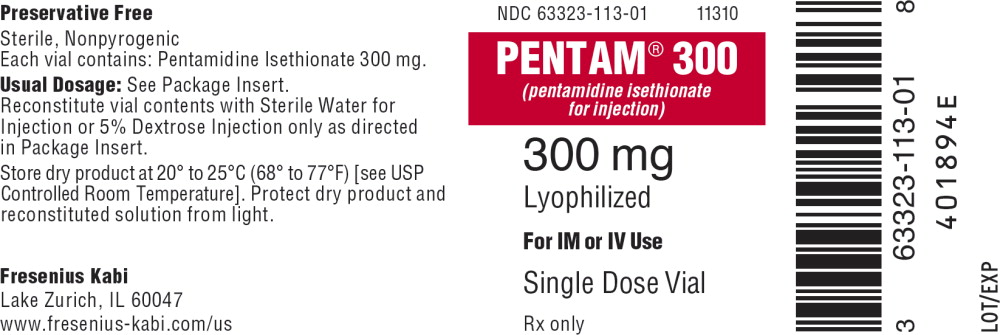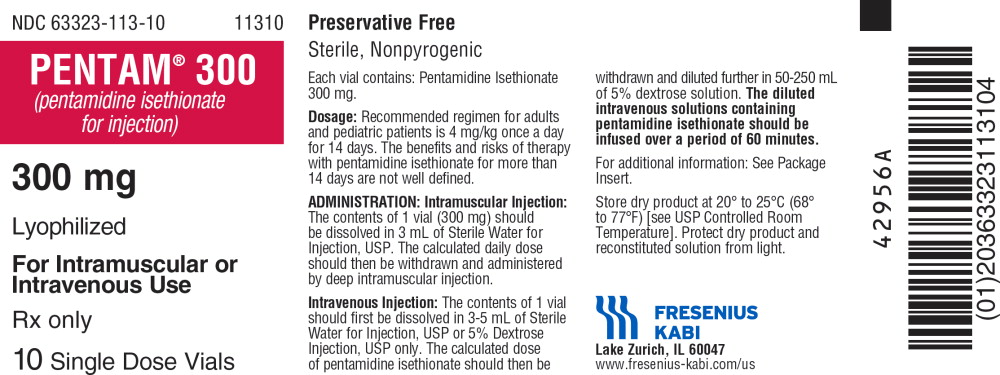 DRUG LABEL: Pentam 300
NDC: 63323-113 | Form: INJECTION, POWDER, LYOPHILIZED, FOR SOLUTION
Manufacturer: Fresenius Kabi USA, LLC
Category: prescription | Type: HUMAN PRESCRIPTION DRUG LABEL
Date: 20220913

ACTIVE INGREDIENTS: PENTAMIDINE ISETHIONATE 300 mg/3 mL

Pentam® 300 (pentamidine isethionate for injection)

For Injection Only

DESCRIPTION

Pentam 300 (pentamidine isethionate for injection), an anti-protozoal agent, is a sterile, nonpyrogenic, lyophilized product. After reconstitution, it should be administered by intramuscular (IM) or intravenous (IV) routes (see DOSAGE AND ADMINISTRATION). Pentamidine isethionate is a white crystalline powder soluble in water and glycerin, slightly soluble in alcohol and insoluble in ether, acetone, and chloroform. It is chemically designated as 4,4-[1,5-pentanediylbis(oxy)]bis-benzenecarboximidamid with the following structural formula:

Each vial contains:
Pentamidine isethionate . . . . . . . . . . . . . 300 mg

CLINICAL PHARMACOLOGY

Pentamidine isethionate, an aromatic diamidine, is known to have activity against Pneumocystis carinii. The mode of action of pentamidine is not fully understood. In vitro studies indicate that the drug interferes with protozoal nuclear metabolism by inhibition of DNA, RNA, phospholipid and protein synthesis.

Pharmacokinetics

Pharmacokinetic parameters following the administration of 4 mg/kg pentamidine isethionate as a single two-hour intravenous infusion or after a single intramuscular injection to 12 patients with AIDS are presented in the following table:

Mean ±; SD | Cmax; ng/mL | Clearance; L/h | Half-life; hours | Vdss; L | Concentration; ng/mL
Mean ±; SD | Cmax; ng/mL | Clearance; L/h | Half-life; hours | Vdss; L | 8 hour | 24 hour
2 hour I.V. infusion; 4 mg/kg (N=6) | 612 ± 371 | 248 ± 91 | 6.4 ± 1.3 | 821 ± 535 | 19.3 ± 16.9 | 2.9 ± 1.4
I.M.; 4 mg/kg (N=6) | 209 ± 48 | 305 ± 81 | 9.4 ± 2.0 | 2724 ± 1066 | 22.9 ± 8.0 | 6.6 ± 3.5

In seven patients treated with daily IM doses of pentamidine at 4 mg/kg for 10 to 12 days, plasma concentrations were between 300 to 500 ng/mL. The concentrations did not appreciably change with time after injection or from day to day. Higher plasma concentrations were encountered in patients with an elevated blood urea nitrogen. The patients continued to excrete decreasing amounts of pentamidine in urine up to 6 to 8 weeks after cessation of the treatment.

Following multiple intravenous administration of pentamidine isethionate (3.7 to 4 mg/kg/day infused over 4 hours) to 6 patients with AIDS being treated for PCP, the pharmacokinetic parameters obtained on Days 1,4 and 7 are summarized in the following table:

Mean; ± SD | Cmax*; ng/mL | Cmin*; ng/mL | Clearance; mL/min | Renal Clearance mL/min/1.73 m^2 | Creatinine Clearance mL/min/1.73 m^2
Day 1 | 175.3 ± 54 | --- | 5737 ± 1878 | 269 ± 149 | 97 ± 12
Day 4 | 210.9 ± 80 | 17.6 ± 9.5 | 3350 ± 1944 | 214 ± 145 | 93 ± 17
Day 7 | 256.7 ± 89 | 40.8 ± 16.1 | 1989 ± 566 | 134 ± 60 | 69 ± 17

*derived from Lidman

Compared to the mean AUC on Day 1, AUC on Day 4 and Day 7 were about 2 and 3 fold higher, respectively, suggesting that steady state was not achieved by Day 7 of dosing.

In other published reports of pharmacokinetics of pentamidine following daily intravenous doses of 2 to 4 mg/kg/day, clearance ranged from 30 to 40 mL/min/kg and Vdss ranged from 200 to 400 L/kg. Reported values for terminal half-lives of 2.8 to 12 days is suggestive of a deep peripheral compartment. In the urine, up to 12% of the administered dose has been recovered during a dosing interval as unchanged pentamidine.

Tissue distribution was studied in mice given a single intraperitoneal injection of pentamidine at 10 mg/kg. The concentration was highest in the kidneys followed by the liver. In mice, pentamidine was excreted unchanged, primarily via the kidneys with some elimination in the feces. The ratio of amounts excreted in the urine and feces (4:1) was constant over the period of study.

Tissue distribution has also been studied in normal and in renally impaired dogs (N = 3 each) given 13 mg/kg of pentamidine IV, in 2 doses separated by five weeks. The concentration of pentamidine was highest in the liver followed by kidneys and lungs. Pentamidine was concentrated in these organs approximately 70 to 1000 times that of the peak serum concentration. Similar findings were reported in normal and in renally impaired dogs (N = 2 each) given 97.5 mg/kg of pentamidine IV, in 15 daily doses. After repeated doses, the organs showed a further 3 to 7 fold accumulation while serum concentrations remained unchanged.

INDICATIONS AND USAGE

Pentam 300 (pentamidine isethionate for injection) is indicated for the treatment of pneumonia due to Pneumocystis carinii.

CONTRAINDICATIONS

Contraindicated in patients with a history of hypersensitivity to pentamidine isethionate.

WARNINGS

Fatalities due to severe hypotension, hypoglycemia, acute pancreatitis and cardiac arrhythmias have been reported in patients treated with pentamidine isethionate, both by the IM and IV routes. Severe hypotension may result after a single IM or IV dose and is more likely with rapid IV administration (see PRECAUTIONS). The administration of the drug should, therefore, be limited to the patients in whom Pneumocystis carinii has been demonstrated. Patients should be closely monitored for the development of serious adverse reactions (see PRECAUTIONS and ADVERSE REACTIONS).

Extravasations have been reported which, in some instances, proceeded to ulceration, tissue necrosis and/or sloughing at the injection site. While not common, surgical debridement and skin grafting has been necessary in some of these cases; long-term sequelae have been reported. Prevention is the most effective means of limiting the severity of extravasation. The intravenous needle or catheter must be properly positioned and closely observed throughout the period of pentamidine isethionate administration. If extravasation occurs, the injection should be discontinued immediately and restarted in another vein. Because there are no known local treatment measures which have proven to be useful, management of the extravasation should be symptomatic.

PRECAUTIONS

General

Pentamidine isethionate should be used with caution in patients with hypertension, hypotension, ventricular tachycardia, hypoglycemia, hyperglycemia, hypocalcemia, pancreatitis, leukopenia, thrombocytopenia, anemia, hepatic or renal dysfunction and Stevens-Johnson syndrome.

Patients may develop sudden, severe hypotension after a single dose of pentamidine isethionate, whether given IV or IM. Therefore, patients receiving the drug should be lying down and the blood pressure should be monitored closely during administration of the drug and several times thereafter until the blood pressure is stable. Equipment for emergency resuscitation should be readily available. If pentamidine isethionate is administered IV, it should be infused over a period of 60 to 120 minutes.

Pentamidine isethionate-induced hypoglycemia has been associated with pancreatic islet cell necrosis and inappropriately high plasma insulin concentrations. Hyperglycemia and diabetes mellitus, with or without preceding hypoglycemia, have also occurred, sometimes several months after therapy with pentamidine isethionate. Therefore, blood glucose levels should be monitored daily during therapy with pentamidine isethionate, and several times thereafter.

Renal and Hepatic Impairment

The efficacy or safety of alternative Pentam 300 dosing protocols have not been established for patients with impaired renal or hepatic function.

Laboratory Tests

The following tests should be carried out before, during and after therapy:

a) Daily blood urea nitrogen and serum creatinine determinations.

b) Daily blood glucose determinations.

c) Complete blood count and platelet count.

d) Liver function test, including serum bilirubin, alkaline phosphatase, AST (SGOT), and ALT (SGPT).

e) Serum calcium determinations.

f) Electrocardiograms.

Drug Interactions

No drug interaction studies with Pentam 300 have been conducted.

Because the nephrotoxic effects may be additive, the concomitant or sequential use of pentamidine isethionate and other nephrotoxic drugs such as aminoglycosides, amphotericin B, cisplatin, foscarnet, or vancomycin should be closely monitored and avoided, if possible.

Carcinogenesis, Mutagenesis, Impairment of Fertility

No studies have been conducted to evaluate the potential of pentamidine isethionate as a carcinogen, mutagen, or cause of impaired fertility.

Pregnancy-Pregnancy Category C

Animal reproduction studies have not been conducted with pentamidine isethionate. It is also not known whether pentamidine isethionate can cause fetal harm when administered to a pregnant woman or can affect reproduction capacity. Pentamidine isethionate should not be given to a pregnant woman unless the potential benefits are judged to outweigh the unknown risks.

Nursing Mothers

It is not known whether pentamidine isethionate is excreted in human milk. Because of the potential for serious adverse reactions in nursing infants from pentamidine isethionate, a decision should be made whether to discontinue nursing or to discontinue the drug, taking into account the importance of the drug to the mother. Because many drugs are excreted in human milk, pentamidine isethionate should not be given to a nursing mother unless the potential benefits are judged to outweigh the unknown risks.

Pediatric Use

Intravenous and intramuscular pentamidine has been described as an effective treatment for Pneumocystis carinii pneumonia (PCP) in immunocompromised pediatric patients beyond 4 months of age. The efficacy and safety profiles in these pediatric patients were similar to those observed in adult patients (See DOSAGE AND ADMINISTRATIONand OVERDOSAGE) .

ADVERSE REACTIONS

To report SUSPECTED ADVERSE REACTIONS, contact Fresenius Kabi USA, LLC at 1-800-551-7176 or FDA at 1-800-FDA-1088 or www.fda.gov/medwatch.

CAUTION: Fatalities due to severe hypotension, hypoglycemia, acute pancreatitis and cardiac arrhythmias have been reported in patients treated with pentamidine isethionate, both by the IM and IV routes. Nephrotoxic events (increased creatinine, impaired renal function, azotemia, and renal failure) are common with the parenteral administration of pentamidine isethionate. The administration of the drug should, therefore, be limited to the patients in whom Pneumocystis carinii has been demonstrated.

The most frequently reported spontaneous adverse events (1 to 30%) reported in clinical trials, regardless of their relation to pentamidine isethionate therapy were as follows (n=424):

Cardiovascular:; Hypotension | 5.0%
Gastrointestinal:; Anorexia/Nausea | 5.9%
Hematologic:; Anemia; Leukopenia; Thrombocytopenia | 1.2%; 10.4%; 2.6%
Hepatic:; Elevated liver function tests | 8.7%
Metabolic:; Hypoglycemia | 5.9%
Neurologic:; Confusion/hallucinations | 1.7%
Skin:; Sterile abscess and/or necrosis,; pain, or induration at the site of; IM injection; Rash | 11.1%; 3.3%
Special Senses:; Bad taste | 1.7%
Urogenital:; Azotemia; Elevated serum creatinine; Elevated blood urea nitrogen; Impaired renal function | 8.5%; 23.6%; 6.6%; 28.8%

Adverse events with a frequency of less than 1% incidence were as follows (No causal relationship to treatment has been established for these adverse events):

Body as a whole: | Allergic reaction (i.e. urticaria, itching, rash), anaphylaxis, arthralgia, chills, extrapulmonary pneumocystosis, headache, night sweats, and Stevens-Johnson syndrome.
Cardiovascular: | Abnormal ST segment of electrocardiogram, cardiac arrhythmias, cerebrovascular accident, hypertension, palpitations, phlebitis, syncope, tachycardia, vasodilatation, vasculitis and ventricular tachycardia.
Gastrointestinal: | Abdominal pain, diarrhea, dry mouth, dyspepsia, hematochezia, hypersalivation, melena, pancreatitis, splenomegaly, and vomiting.
Hematological: | Defibrination, eosinophilia, neutropenia, pancytopenia, and prolonged clotting time.
Hepatic: | Hepatic dysfunction, hepatitis and hepatomegaly
Metabolic: | Hyperglycemia, hyperkalemia, hypocalcemia, and hypomagnesemia.
Neurological: | Anxiety, confusion, depression, dizziness, drowsiness, emotional lability, hypesthesia, insomnia, memory loss, neuropathy, nervousness, neuralgia, paranoia, paresthesia, peripheral neuropathy, seizure, tremors, unsteady gait, and vertigo.
Respiratory system: | Asthma, bronchitis, bronchospasm, chest congestion, chest tightness, coryza, cyanosis, eosinophilic or interstitial pneumonitis, gagging, hemoptysis, hyperventilation, laryngitis, laryngospasm, non-specific lung disorder, nasal congestion, pleuritis, pneumothorax, rales, rhinitis, shortness of breath, and tachypnea.
Skin: | Desquamation, dry and breaking hair, dry skin, erythema, dermatitis, pruritus, rash, and urticaria.
Special senses: | Blepharitis, blurred vision, conjunctivitis, contact lens discomfort, eye pain or discomfort, loss of hearing, loss of taste, and loss of smell.
Urogenital: | Flank pain, hematuria, incontinence, nephritis, renal dysfunction and renal failure.

From post-marketing clinical experience with pentamidine isethionate, the following adverse events have been reported: cough, diabetes mellitus/ketoacidosis, dyspnea, infiltration (extravasation–see WARNINGS), and torsades de pointes.

OVERDOSAGE

A 17 month old infant inadvertently received 1600 mg of intravenous pentamidine isethionate which was followed by renal and hepatic function impairment, hypotension and cardiopulmonary arrest. Treatment included cardiopulmonary resuscitation, epinephrine, atropine and intubation. In addition, a four hour course of charcoal hemoperfusion was accompanied by reduction of pentamidine serum concentration and stabilization of the patient’s condition. The patient recovered from these adverse events, but later died due to an unknown cause.^1

DOSAGE AND ADMINISTRATION

CAUTION: DO NOT USE SODIUM CHLORIDE INJECTION, USP FOR INITIAL RECONSTITUTION BECAUSE PRECIPITATION WILL OCCUR. Pentamidine isethionate should be administered IM or IV only. The recommended regimen for adults and pediatric patients beyond 4 months of age is 4 mg/kg once a day for 14 to 21 days. Therapy for longer than 21 days with pentamidine isethionate has also been used but may be associated with increased toxicity.

Intramuscular Injection

The contents of one vial (300 mg) should be dissolved in 3 mL of Sterile Water for Injection, USP at 22° - 30°C (72° - 86°F). The calculated daily dose should then be withdrawn and administered by deep IM injection.

Intravenous Injection

The contents of one vial (300 mg) should first be dissolved in 3 to 5 mL of Sterile Water for Injection, USP, or 5% Dextrose Injection, USP at 22°- 30°C (72° - 86°F). The calculated dose of pentamidine isethionate should then be withdrawn and diluted further in 50 to 250 mL of 5% Dextrose Injection, USP.

The diluted IV solutions containing pentamidine isethionate should be infused over a period of 60 to 120 minutes.

Aseptic technique should be employed in preparation of all solutions. Parenteral drug products should be inspected visually for particulate matter and discoloration prior to administration whenever solution and container permit.

Stability

After reconstitution with sterile water, the Pentam solution is stable for 48 hours in the original vial at room temperature if protected from light. To avoid crystallization,store at 22° - 30°C (72° - 86°F). Intravenous infusion solutions of pentamidine isethionate at 1 mg/mL and 2.5 mg/mL prepared in 5% Dextrose Injection, USP are stable at room temperature for up to 24 hours.

Intravenous (IV) solutions of pentamidine isethionate have been shown to be incompatible with fluconazole and foscarnet sodium. IV solutions of pentamidine isethionate have been shown to be compatible with IV solutions of zidovudine (AZT) and diltiazem hydrochloride.

HOW SUPPLIED

PENTAM® 300 (pentamidine isethionate for injection)

Product Code | Unit of Sale | Strength | Each
11310 | NDC 63323-113-10 Unit of 10 | 300 mg | NDC 63323-113-01 Lyophilized Product in Single Dose Vial

Store dry product at 20° to 25°C (68° to 77°F) [see USP Controlled Room Temperature]. Protect from light.

Preservative Free. Discard unused portion.

REFERENCE

1. Watts RG; Conte JE, Jr.; Zurlinden E; Waldo FB: Effect of charcoal hemoperfusion on clearance of pentamidine isethionate after accidental overdose. J Toxicol Clin Toxicol 1997;35:89-92.

www.fresenius-kabi.com/us

45851D

Revised: May 2022

PACKAGE LABEL

PACKAGE LABEL - PRINCIPAL DISPLAY – Pentam® 300 mg Single Dose Vial Label

NDC 63323-113-01 11310

PENTAM® 300

(pentamidine isethionate for injection)

300 mg

Lyophilized

For IM or IV Use

Single Dose Vial

Rx only

PACKAGE LABEL

PACKAGE LABEL - PRINCIPAL DISPLAY – Pentam® 300 mg Single Dose Tray Label

NDC 63323-113-10 11310

PENTAM® 300

(pentamidine isethionate for injection)

300 mg

Lyophilized

For Intramuscular or

Intravenous Use

Rx only

10 Single Dose Vials